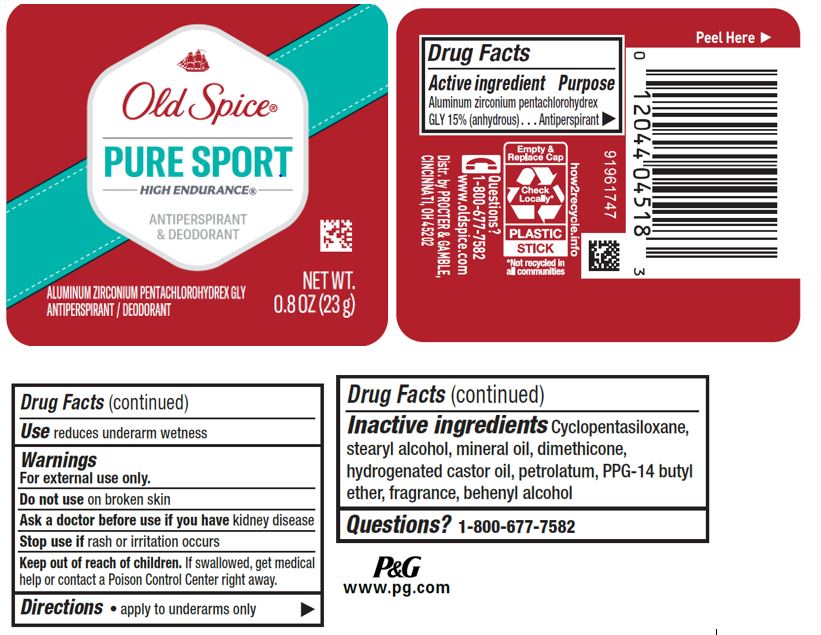 DRUG LABEL: Old Spice Pure Sport High Endurance
NDC: 69423-611 | Form: STICK
Manufacturer: The Procter & Gamble Manufacturing Company
Category: otc | Type: HUMAN OTC DRUG LABEL
Date: 20251218

ACTIVE INGREDIENTS: ALUMINUM ZIRCONIUM PENTACHLOROHYDREX GLY 15 g/100 g
INACTIVE INGREDIENTS: 2-ETHYL-4-(2,2,3-TRIMETHYLCYCLOPENT-3-EN-1-YL)BUT-2-EN-1-OL; ISOPROPYL MYRISTATE; 2-ISOBUTYL-4-METHYLTETRAHYDROPYRAN-4-OL; HEXAMETHYLINDANOPYRAN; ISOMETHYL-.ALPHA.-IONONE; PHENYLETHYL ALCOHOL; POGOSTEMON CABLIN LEAF OIL; AMYL SALICYLATE; ANETHOLE; .BETA.-PINENE, (-)-; .ALPHA.-HEXYLCINNAMALDEHYDE; LINALYL ACETATE; METHYL DIHYDROJASMONATE (SYNTHETIC); ORANGE TERPENES; CEDRAMBER; ORANGE OIL; DIPROPYLENE GLYCOL; EUGENOL; GERANIOL; 3-(3,4-METHYLENEDIOXYPHENYL)-2-METHYLPROPANAL; .BETA.-CITRONELLOL, (R)-; BERGAMOT OIL; LEMON; ALLYL AMYL GLYCOLATE; LIMONENE, (+)-; PRECYCLEMONE B; MANDARIN OIL; CORIANDER OIL; PENTADECALACTONE; ACETYL HEXAMETHYL TETRALIN; ACETYL CEDRENE; BENZYL SALICYLATE; CITRAL; COUMARIN; TRIETHYL CITRATE; DIMETHICONE; CYCLOMETHICONE 5; STEARYL ALCOHOL; PPG-14 BUTYL ETHER; DIHYDROMYRCENOL; HYDROGENATED CASTOR OIL; PETROLATUM; MINERAL OIL; DOCOSANOL; TETRAMETHYL ACETYLOCTAHYDRONAPHTHALENES; .GAMMA.-TERPINENE; LAVANDIN OIL; CYCLAMEN ALDEHYDE

Old Spice® Pure Sport High Endurance® Wide Solid

Drug Facts

Active ingredient

Aluminum zirconium pentachlorohydrex Gly 15% (anhydrous)

Purpose

Antiperspirant

Use

reduces underarm wetness

Warnings

For external use only.

Do not use on broken skin

Ask a doctor before use if you have kidney disease

Stop use if rash or irritation occurs

Keep out of reach of children. If swallowed, get medical help or contact a Poison Control Center right away.

Directions

- apply to underarms only

Inactive ingredients

cyclopentasiloxane, stearyl alcohol, mineral oil, dimethicone, hydrogenated castor oil, petrolatum, PPG-14 butyl ether, fragrance, behenyl alcohol

Questions?

1-800-677-7582

Dist. by PROCTER & GAMBLE, CINCINNATI, OH 45202.

PRINCIPAL DISPLAY PANEL - 85 g Canister Label

Old Spice®

PURE SPORT

HIGH ENDURANCE®

ANTIPERSPIRANT
& DEODORANT

Aluminum Zirconium Pentachlorohydrex Gly
ANTIPERSPIRANT/DEODORANT

NET WT. .8 OZ (23 g)